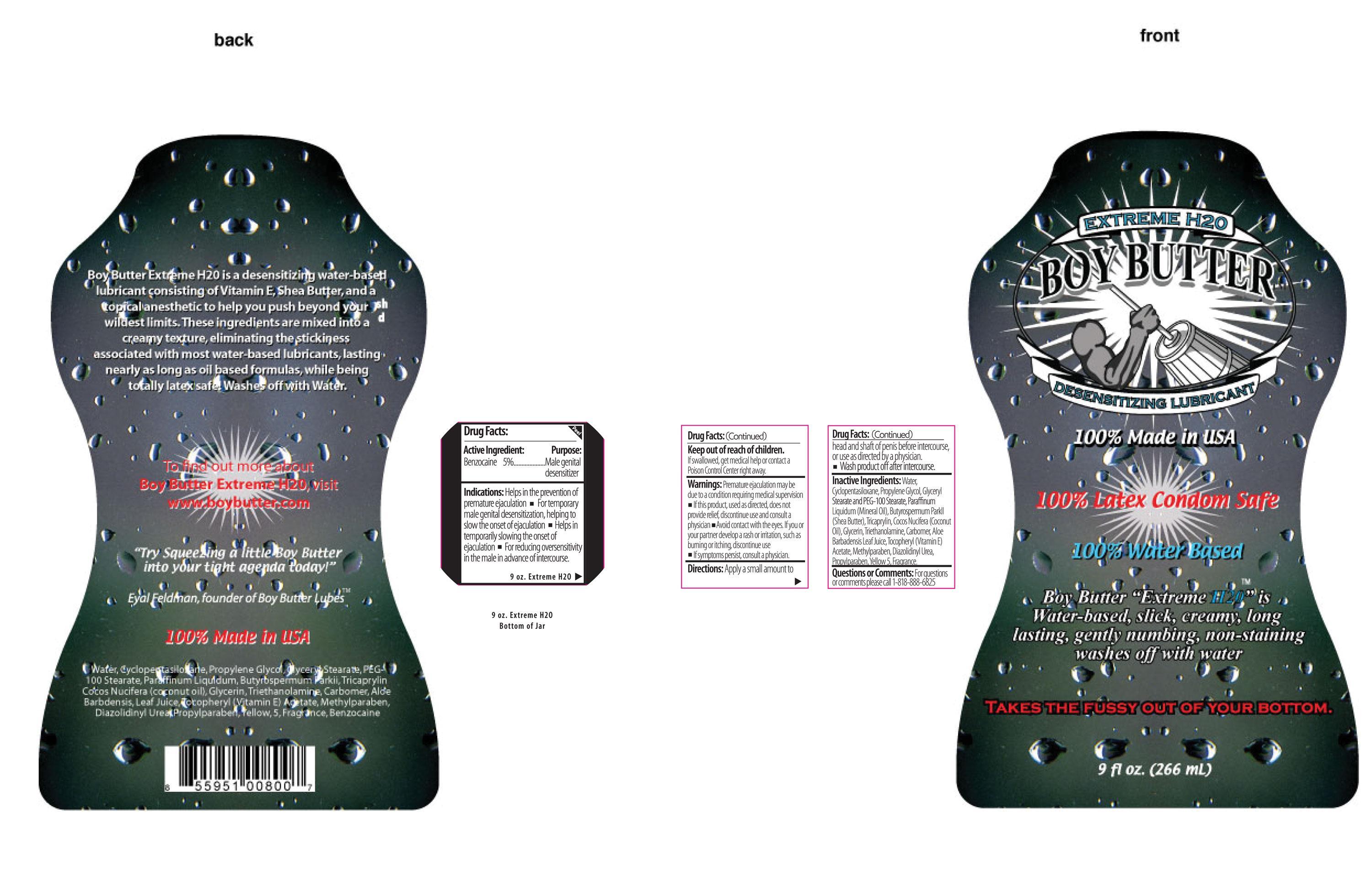 DRUG LABEL: Boy Butter
NDC: 24488-042 | Form: CREAM
Manufacturer: Boy Butter Lubes
Category: otc | Type: HUMAN OTC DRUG LABEL
Date: 20120925

ACTIVE INGREDIENTS: BENZOCAINE 73.9395789 mg/1 mL
INACTIVE INGREDIENTS: WATER; CYCLOMETHICONE 5; PROPYLENE GLYCOL; GLYCERYL MONOSTEARATE; MINERAL OIL; SHEA BUTTER; TRICAPRYLIN; COCONUT OIL; GLYCERIN; TROLAMINE; CARBOMER HOMOPOLYMER TYPE C; ALOE VERA LEAF; .ALPHA.-TOCOPHEROL ACETATE; METHYLPARABEN; DIAZOLIDINYL UREA; PROPYLPARABEN; FD&C YELLOW NO. 5

Drug Facts:

Active Ingredient:

Benzocaine 7.5%

Purpose

Male genital desensitizer

Indications:

Helps in the prevention of premature ejaculation.

- For temporary male genital desensitization, helping to slow the onset of ejaculation
- Helps in temporarily slowing the onset of ejaculation
- For reducing oversensitivity in the male in advancer of intercourse.

Keep out of reach of children

If swallowed, get medical help or contact a
Poison Control Center right away.

Warnings:

Premature ejaculation may be due to a condition requiring medical supervision.

- If this product, used as directed, does not provide relief, discontinue use and consult a physician
- Avoid contact with the eye. If you or your partner develop a rash or irritation, such as burning or itching, discontinue use
- If symptoms persist, consult a physician.

Directions:

Apply a small amount to head and shaft of penis before intercourse, or use as directed by a physician

- Wash product off after intercourse

Inactive Ingredients:

Error: java.security.PrivilegedActionException: net.sf.saxon.xpath.DynamicError: org.xml.sax.SAXParseException; lineNumber: 1; columnNumber: 183; An invalid XML character (Unicode: 0x1e) was found in the element content of the document.

Questions or Comments:

For questions or comments, please call 1-818-888-6825

PACKAGE LABEL

Placeholder Text